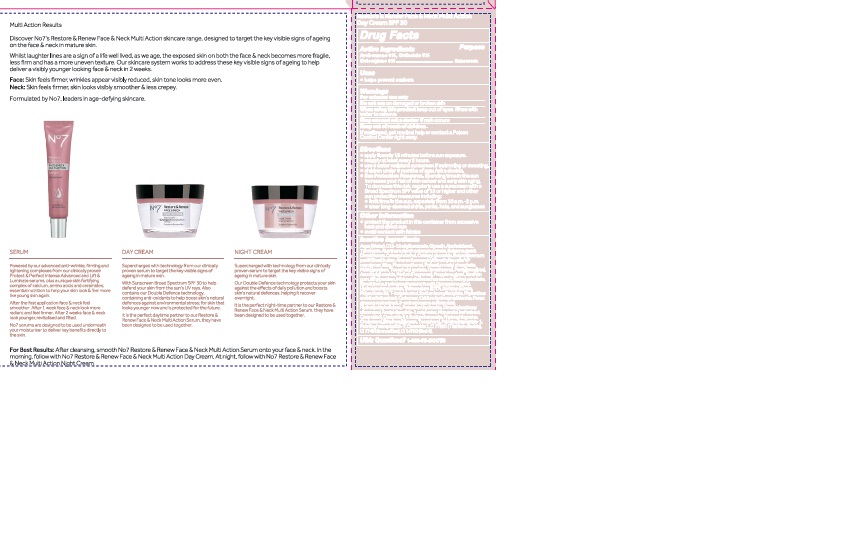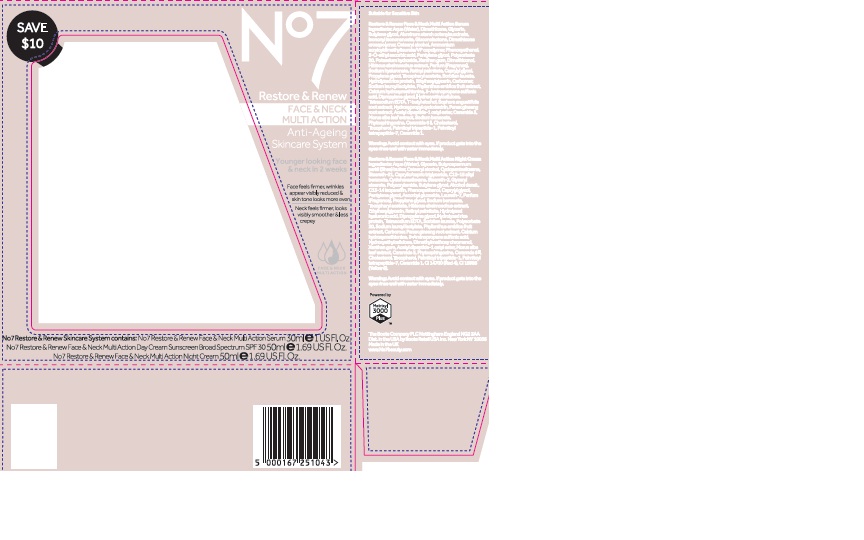 DRUG LABEL: No7Restore and Renew Face and Neck Multi Action Day Cream Sunscreen Broad Spectrum SPF 30
NDC: 11489-128 | Form: CREAM
Manufacturer: BCM Ltd
Category: otc | Type: HUMAN OTC DRUG LABEL
Date: 20180228

ACTIVE INGREDIENTS: AVOBENZONE 1.5 g/1 g; OCTOCRYLENE 4.0 g/1 g; OCTISALATE 2.5 g/1 g
INACTIVE INGREDIENTS: WATER; GLYCERIN; ALUMINUM STARCH OCTENYLSUCCINATE; CETEARYL GLUCOSIDE; DIMETHICONE; TRIBEHENIN; AMMONIUM ACRYLOYLDIMETHYLTAURATE/VP COPOLYMER; PHENOXYETHANOL; SHEA BUTTER; POTASSIUM CETYL PHOSPHATE; BUTYLENE GLYCOL; DIMETHICONOL (100000 CST); PROPYLENE GLYCOL; METHYLPARABEN; PENTYLENE GLYCOL; ETHYLPARABEN; DIPROPYLENE GLYCOL; SODIUM LAUROYL LACTYLATE; PHYLLANTHUS EMBLICA FRUIT; XANTHAN GUM; HYDROXYETHYL CELLULOSE (100 MPA.S AT 2%); PANAX GINSENG ROOT OIL; VITAMIN A PALMITATE; ASCORBYL GLUCOSIDE; EDETATE SODIUM; TERT-BUTYL ALCOHOL; DIMETHYLMETHOXY CHROMANOL; N-ACETYL DIPEPTIDE-1; POLYSORBATE 20; POTASSIUM HYDROXIDE; CARBOMER 940; MORUS ALBA LEAF; CERAMIDE 3; SODIUM BENZOATE; PHYTOSPHINGOSINE; CERAMIDE 6 II; CHOLESTEROL; ETHYLHEXYLGLYCERIN; TOCOPHEROL; CERAMIDE 1; TITANIUM DIOXIDE; BROWN IRON OXIDE; PALMITOYL TRIPEPTIDE-1; PALMITOYL TETRAPEPTIDE-7

No7 Restore and Renew Face and Neck Multi Action Day Cream Sunscreen Broad Spectrum SPF 30

Carton Active Ingredients Section

Active ingredients

Avobenzone 3%

Octisalate 5%

Octocrylene 8%

Uses

Uses - helps prevent sunburn

Warnings

For external use only

Do not use on damaged or broken skin

When using this product keep out of eyes. Rinse with water to remove.

Ask a doctor

Stop use and ask a doctor if rash occurs

Keep out of reach of children

If swallowed, get medical help or contact a Poison Control Center right away

Directions

Apply liberally 15 minutes before sun exposure

reapply at least every 2 hours

use a water resistant sunscreen if swimming or sweating

children under 6 months of age: Ask a doctor

Sun Protection Measures. Spending time in the sun increases your risk of skin cancer and early skin aging.

To decrease this risk, regularly use a sunscreen with a Broad Spectrum SPF value of 15 or higher and other sun protection measures including:

Limit time in the sun, especially from 10 a.m - 2 p.m.

wear long-sleeved shirts,pants,hats and sunglasses.

Storage

Other information

Protect the product in this container from excessive heat and direct sun

Avoid contact with fabrics

Inactive ingredients

Aqua(Water), Glycerin, C12-15 alkyl benzoate,Tribehenin, Alcohol denat, Dimethicone, Aluminum starch octenylsuccinate, Butylene glycol, Cetearyl alcohol, Cetearyl glucoside, Butyrospermum parkii(Shea)butter, Ammonium acryloydimethyltaurate/VP copolymer, Phenoxyethanol, Potassium cetyl phosphate, Methylparaben, Parfum(Fragrance), Dimethiconol, Pentylene glycol, Propylene glycol, Xanthan gum, Tocopheryl acetate, Ascorbyl glucoside, Ethylparaben, Hibiscus abelmoschus extract, Retinyl palmitate, Simethicone, Hydrolyzed hyaluronic acid, Dipropylene glycol, Hydrolyzed rice protein, Tetrasodium EDTA, Sorbitan laurate, T-butyl alcohol, Sodium lauroyl lactylate, Phyllanthus emblica fruit extract, Calcium hydroxymethionine, 3-aminopropane sulfonic acid, Hydroxyethylcellulose, Acetyl dipeptide-1 cetyl ester, Ceramide 3, Ceramide 6 11,

Panax ginseng root extract, Dimethylmethoxy chromanol, Carbomer, Potassium hydroxide, Polysorbate 20, Morus alba leaf extract, Silica, Sodium benzoate, Phytosphingsine, Cholesterol,Tocopherol, Ethylhexylglycerin, Palmitoyl tripeptide-1, Palmitoyl tetrapeptide-7, Ceramide 1, CI 77891(Titanium dioxide), CI 77491 (Iron oxides) CI 14700(Red 4)

Description

No7 Restore and Renew Face and Neck Multi Action Anti-Ageing Skincare System

Younger looking face and neck in 2 weeks

Face feels firmer, wrinkles appear visibly reduced and skin tone looks more even

Neck feels firmer, looks visibly smoother and less crepey

No7 Restore and Renew Skincare System contains: No7 Restore and Renew Face and Neck Multi Action Serum 30ml e1 US Fl.Oz. No7 Restore and Renew Face and Neck Multi Action Day Cream Sunscreen Broad Spectrum SPF 30 50ml e 1.69 US Fl.Oz. No7 Restore and Renew Face and Neck Multi Action Night Cream 50ml e 1.69 US Fl.Oz.

Description

Multi Action Results

Discover No7's Restore and Renew Face and Neck Multi Action skincare range, designed to target the key visible signs of ageing on the face and neck in mature skin.

Whilst laughter lines are a sign of a life well lived, as we age, the exposed skin on both the face and neck becomes more fragile, less firm and has a more uneven texture. Our skincare sysem works to address these key visible signs of ageing to help deliver a visibly younger looking face and neck in 2 weeks.

Face: Skin feels firmer, wrinkles appear visibly reduced, skin tone looks more even.

Neck: Skin feels firmer, skin looks visibly smoother and less crepey.

Formulated by No7, leaders in age-defying skincare.

SERUM

Powered by our advanced anti-wrinkle, firming and lightening complexes from our clinically proven Protect and Perfect Intense Advanced and Lift and Luminate serums, plus a unique skin fortifying complex of calcium, amino acids and ceramides; essential nutrition to help your skin look and feel more like young skin again.

After the first application face and neck feel smoother. After 1 week face and neck look more radiant and feel firmer. After 2 weeks face and neck look younger, revitalised and lifted.

No7 serums are designed to be used underneath your moisturiser to deliver key benefits directly to the skin.

DAY CREAM

Supercharged with technology from our clinically proven serum to target the key visible signs of ageing in mature skin.

With Sunscreen Broad Spectrum SPF 30 to help defend your skin from the sun's UV rays. Also contains our Double Defence technology, containing anti-oxidants to help boost skin's natural defences against environmental stress; for skin that looks younger now and is protected for the future. It is the perfect daytime partner to our Restore and Renew Face and Neck Multi Action Serum, they have been designed to be used together.

NIGHT CREAM

Supercharged with technology from our clinically proven serum to target the key visible signs of ageing in mature skin.

Our Double Defence technology protects your skin against the effects of daily pollution and boosts skin's natural defences, helping it recover overnight.

It is the perfect night-time partner to our Restore and Renew Face and Neck Multi Action Serum, they have been designed to be used together.

For Best Results: After cleansing, smooth No7 Restore and Renew Face and Neck Multi Action Serum onto your face and neck. In the morning, follow with No7 Restore and Renew Face and Neck Multi Action Day Cream. At night, follow with No7 Restore and Renew Face and Neck Multi Action Night Cream.

PATIENT COUNSELING INFORMATION

The Boots Company PLC Nottingham England NG2 3AA

Dist. in the USA by Boots Retail USA Inc. New York NY 10005

Made in the UK

www.No7beauty.com